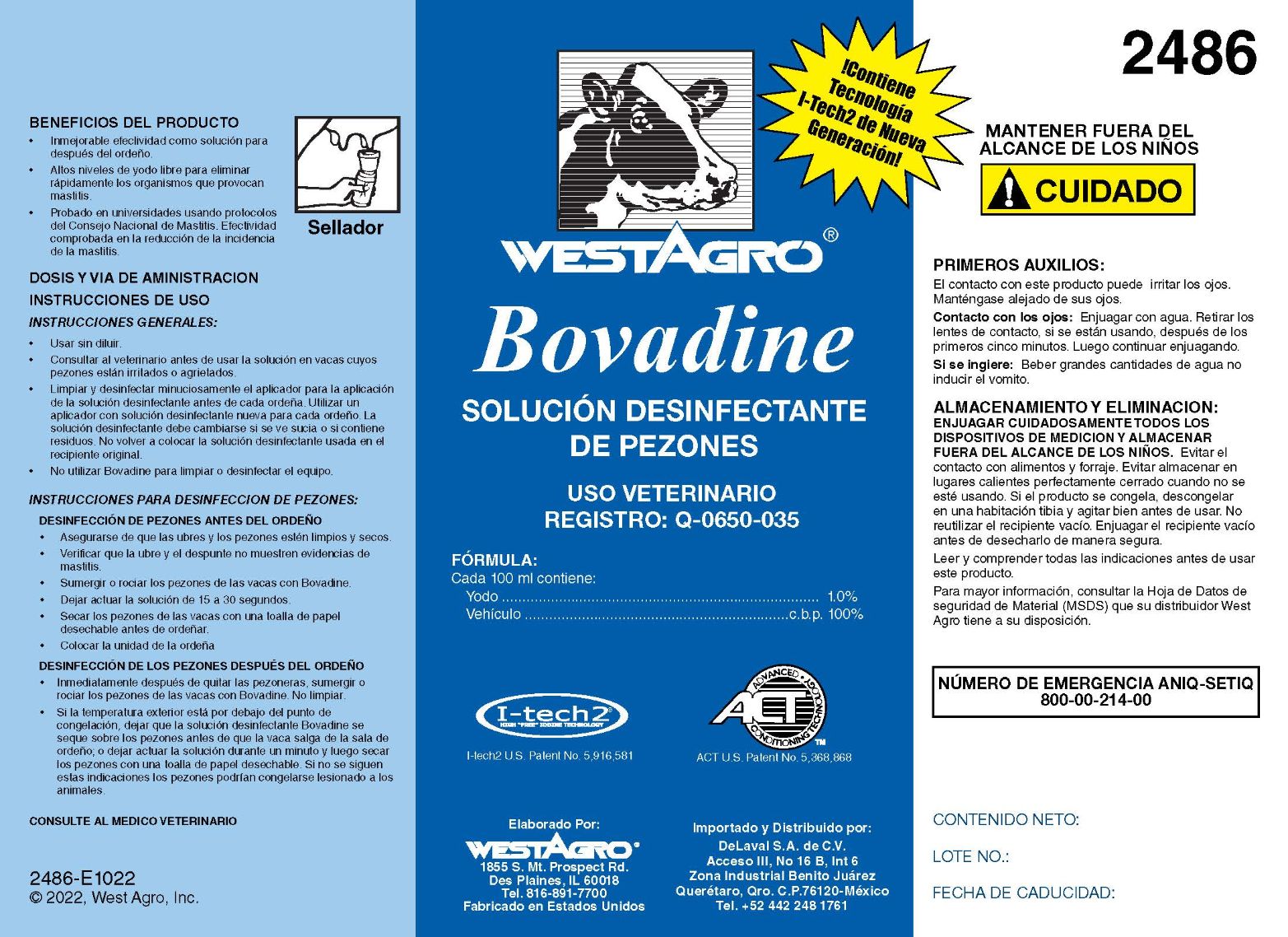 DRUG LABEL: Bovadine
NDC: 33392-486 | Form: SOLUTION
Manufacturer: WestAgro, Inc.
Category: animal | Type: OTC ANIMAL DRUG LABEL
Date: 20240920

ACTIVE INGREDIENTS: IODINE 10.5 g/1 L

WESTAGRO Bovadine

SANITIZING TEAT DIP
with 10% Glycerin

Sellador De Pezones Desinfectante Con Glicerina

ACTIVE INGREDIENT:
Iodine ......................................................... 1.0%
From Polyethoxy polypropoxy polyethoxy ethanol-iodine Complex

I-tech2
HIGH "FREE" IODINE TECHNOLOGY

U.S. Patent No. 5,916,581

NPE FREE Formula

ACT
ADVANCED CONDITIONING TECHNOLOGY

U.S. Patent No. 5,368,868

Manufactured by:
WESTAGRO
11100 N. Congress Ave. Kansas City, MO
64153-1296

PRODUCT BENEFITS

- Unsurpassed effectiveness as a post-dip.
- Elevated free iodine for fast kill of mastitis-causing organisms.
- Unique gentle formula has 10% glycerin plus cosmetic-grade complexors to help soften cracked and chapped teats.
- University tested using National Mastitis Council protocols. Proven effective in reducing the incidence of mastitis.

INDICATIONS AND USAGE

DIRECTIONS FOR USE:
GENERAL INSTRUCTIONS

- Use at full strength. Do not dilute.
- Consult your veterinarian before using teat dip on a cow with sore or chapped teats.
- Thoroughly clean and sanitize teat dip cup before each milking. Use fresh teat dip for each milking. Dip solution should be changed if it becomes visibly dirty, or if sediment is introduced. Do not pour used teat dip back into original container.
- Do not use Bovadine teat dip for cleaning or sanitizing equipment.

TEAT DIPPING INSTRUCTIONS
PRE-DIPPING

West Agro recommends the use of Quarter Mate sanitizing teat dip as a predip. However, if you choose to use Bovadine sanitizing teat dip:

- Make sure udder and teats are clean and dry.
- Check foremilk and udder for mastitis.
- Dip or spray cow's teats with Bovadine.
- Allow 15 to 30 seconds contact time.
- Dry cow's teats with a single-service paper towel before milking.
- Attach milker unit.

POST DIPPING

- Immediately after removing inflations, dip or spray cow's teats with Bovadine santizing teat dip. Do not wipe.
- If outside temperature is below freezing, allow Bovadine santizing teat dip to air-dry on cow's teats before cow leaves the parlor; or allow teat dip to remain on cow's teats for one minute, then dry teats with a single service paper towel. Failure to follow these directions may result in frozen teats and injured animals.

Made in USA
0129-H0408
Copyright, 2005, West Agro, Inc.

Contains Next Generation I-Tech 2 Technology!

KEEP OUT OF REACH OF CHILDREN

! CAUTION

MANTENER FUERA DEL ALCANCE DE LOS NINOS

! CUIDADO

SI USTED NO PURDE LEER ESTA ETIQUETA, POR FAVOR PIDA A ALGUIEN MAS QUE SE LA LEA ANTES DE USAR ESTE PRODUCTO

FIRST AID:

Contact with product can cause irritation to eyes. Avoid contact with eyes.
Eye Contact: Flush with water. Remove contact lenses, if present, after first 5 minutes. Then continue flushing.
If Swallowed: Drink large quantities of water and induce vomiting.

THIS PRODUCT IS NOT FOR HUMAN USE

STORAGE AND DISPOSAL:

THOROUGHLY RINSE ALL MEASURING DEVICES AND STORE OUT OF REACH OF CHILDREN. Avoid contact with food or feed. Avoid storing near heat or open flame. Keep container tightly closed when not in use. If product has frozen, thaw in a warm room and shake well before use. Do not reuse empty container. Rinse empty container before disposing in a safe manner.

Read and understand all directions before using this product. For additional information refer to the Material Safety Data Sheet (MSDS) available from your West Agro Dealer.

NÚMERO DE EMERGENCIA ANIQ-SETIQ
800-00-214-00

NET CONTENTS:

LOT NO.:

EXPIRATION DATE:

PACKAGE LABEL

Add image transcription here...

Add image transcription here...